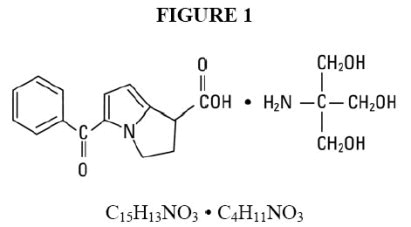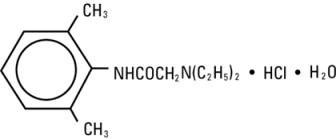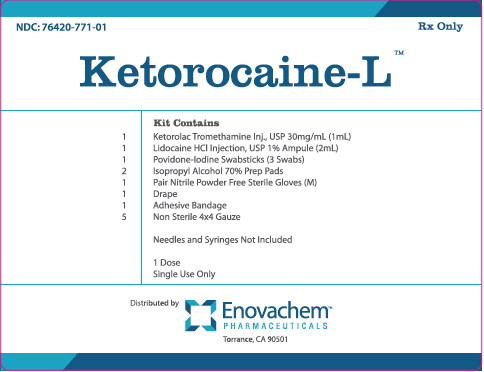 DRUG LABEL: Ketorocaine L Kit
NDC: 76420-771 | Form: KIT | Route: INTRAMUSCULAR
Manufacturer: Asclemed USA, Inc.
Category: prescription | Type: HUMAN PRESCRIPTION DRUG LABEL
Date: 20260108

ACTIVE INGREDIENTS: KETOROLAC TROMETHAMINE 30 mg/1 mL; LIDOCAINE HYDROCHLORIDE 10 mg/1 mL; POVIDONE-IODINE 10 mg/1 mL; ISOPROPYL ALCOHOL 70 mL/100 mL
INACTIVE INGREDIENTS: ALCOHOL 100 mg/1 mL; SODIUM CHLORIDE 4.35 mg/1 mL; HYDROCHLORIC ACID; SODIUM HYDROXIDE; WATER; SODIUM CHLORIDE 7 mg/1 mL; WATER; SODIUM HYDROXIDE; HYDROCHLORIC ACID; GLYCERIN; POLYSORBATE 80; SODIUM CITRATE; SODIUM PHOSPHATE, DIBASIC, ANHYDROUS; CITRIC ACID ACETATE; WATER; WATER

Ketorocaine L Kit

Ketorolac Tromethamine Injection, USP

FOR INTRAVENOUS (IV)/ INTRAMUSCULAR (IM) USE (30 mg)

WARNING

Ketorolac tromethamine, a nonsteroidal anti-inflammatory drug (NSAID), is indicated for the short-term (up to 5 days in adults) management of moderately severe acute pain that requires analgesia at the opioid level. Oral ketorolac tromethamine is indicated only as continuation treatment following intravenous or intramuscular dosing of ketorolac tromethamine, if necessary. The total combined duration of use of oral ketorolac tromethamine and ketorolac tromethamine injection should not exceed 5 days.

Ketorolac tromethamine is not indicated for use in pediatric patients and it is NOT indicated for minor or chronic painful conditions. Increasing the dose of ketorolac tromethamine beyond the label recommendations will not provide better efficacy but will increase the risk of developing serious adverse events.

GASTROINTESTINAL RISK
• Ketorolac tromethamine can cause peptic ulcers, gastrointestinal bleeding and/or perforation of the stomach or intestines, which can be fatal. These events can occur at any time during use and without warning symptoms. Therefore, ketorolac tromethamine is CONTRAINDICATED in patients with active peptic ulcer disease, in patients with recent gastrointestinal bleeding or perforation, and in patients with a history of peptic ulcer disease or gastrointestinal bleeding. Elderly patients are at greater risk for serious gastrointestinal events (see WARNINGS).

CARDIOVASCULAR THROMBOTIC EVENTS

• Nonsteroidal anti-inflammatory drugs (NSAIDs) cause an increased risk of serious cardiovascular thrombotic events, including myocardial infarction and stroke, which can be fatal. This risk may occur early in treatment and may increase with duration of use (see WARNINGSand PRECAUTIONS).
• Ketorolac tromethamine is CONTRAINDICATED in the setting of coronary artery bypass graft (CABG) surgery (see CONTRAINDICATIONSand WARNINGS).
RENAL RISK
• Ketorolac tromethamine is CONTRAINDICATED in patients with advanced renal impairment and in patients at risk for renal failure due to volume depletion (see WARNINGS).
RISK OF BLEEDING
• Ketorolac tromethamine inhibits platelet function and is, therefore, CONTRAINDICATED in patients with suspected or confirmed cerebrovascular bleeding, patients with hemorrhagic diathesis, incomplete hemostasis and those at high risk of bleeding (see WARNINGS and PRECAUTIONS).
Ketorolac tromethamine is CONTRAINDICATED as prophylactic analgesic before any major surgery.
HYPERSENSITIVITY
• Hypersensitivity reactions, ranging from bronchospasm to anaphylactic shock, have occurred and appropriate counteractive measures must be available when administering the first dose of ketorolac tromethamine injection (see CONTRAINDICATIONSand WARNINGS). Ketorolac tromethamine is CONTRAINDICATED in patients with previously demonstrated hypersensitivity to ketorolac tromethamine or allergic manifestations to aspirin or other nonsteroidal anti-inflammatory drugs (NSAIDs).
INTRATHECAL OR EPIDURAL ADMINISTRATION
• Ketorolac tromethamine is CONTRAINDICATED for intrathecal or epidural administration due to its alcohol content.
RISK DURING LABOR AND DELIVERY
• The use of ketorolac tromethamine in labor and delivery is CONTRAINDICATED because it may adversely affect fetal circulation and inhibit uterine contractions.
CONCOMITANT USE WITH NSAIDs
• Ketorolac tromethamine is CONTRAINDICATED in patients currently receiving aspirin or NSAIDs because of the cumulative risk of inducing serious NSAID-related side effects.
SPECIAL POPULATIONS
• Dosage should be adjusted for patients 65 years or older, for patients under 50 kg (110 lbs.) of body weight (see DOSAGE AND ADMINISTRATION) and for patients with moderately elevated serum creatinine (see WARNINGS). Doses of ketorolac tromethamine injection are not to exceed 60 mg (total dose per day) in these patients.
DOSAGE AND ADMINISTRATION
Ketorolac Tromethamine Tablets
• Ketorolac tromethamine tablets are indicated only as continuation therapy to ketorolac tromethamine injection, and the combined duration of use of ketorolac tromethamine injection and ketorolac tromethamine tablets is not to exceed 5 (five) days, because of the increased risk of serious adverse events.
• The recommended total daily dose of ketorolac tromethamine tablets (maximum 40 mg) is significantly lower than for ketorolac tromethamine injection (maximum 120 mg) (see DOSAGE AND ADMINISTRATION).

DESCRIPTION

Ketorolac Tromethamine Injection, USP is a member of the pyrrolo-pyrrole group of nonsteroidal anti-inflammatory drugs (NSAIDs). The chemical name for ketorolac tromethamine is (±)-5-benzoyl-2,3-dihydro-1 H-pyrrolizine-1-carboxylic acid, compound with 2-amino-2-(hydroxymethyl)-1,3-propanediol (1:1), and the structural formula is presented in Figure 1.

C15H13NO3• C4H11NO3
Ketorolac tromethamine is a racemic mixture of [-]S and [+]R ketorolac tromethamine. Ketorolac tromethamine may exist in three crystal forms. All forms are equally soluble in water. Ketorolac tromethamine has a pKa of 3.5 and an n-octanol/water partition coefficient of 0.26. The molecular weight of ketorolac tromethamine is 376.40.
Ketorolac Tromethamine Injection, USP is available for intravenous (IV) or intramuscular (IM) administration as: 15 mg in 1 mL (1.5%) and 30 mg in 1 mL (3%) in sterile solution; 60 mg in 2 mL (3%) of ketorolac tromethamine in sterile solution is available for intramuscular administration only. The solutions contain 10% (w/v) alcohol, USP, and 6.68 mg, 4.35 mg, and 8.70 mg, respectively, of sodium chloride in sterile water. The pH range is 6.9 to 7.9 and is adjusted with sodium hydroxide and/or hydrochloric acid. The sterile solutions are clear to slightly yellow in color.

CLINICAL PHARMACOLOGY

Pharmacodynamics
Ketorolac tromethamine is a nonsteroidal anti-inflammatory drug (NSAID) that exhibits analgesic activity in animal models. The mechanism of action of ketorolac, like that of other NSAIDs, is not completely understood but may be related to prostaglandin synthetase inhibition. The biological activity of ketorolac tromethamine is associated with the S-form.
Ketorolac tromethamine possesses no sedative or anxiolytic properties.
The peak analgesic effect of ketorolac tromethamine occurs within 2 to 3 hours and is not statistically significantly different over the recommended dosage range of ketorolac tromethamine. The greatest difference between large and small doses of ketorolac tromethamine by either route is in the duration of analgesia.

Pharmacokinetics
Ketorolac tromethamine is a racemic mixture of [-]S- and [+]R-enantiomeric forms, with the S-form having analgesic activity.
Comparison of Intravenous, Intramuscular and Oral Pharmacokinetics
The pharmacokinetics of ketorolac tromethamine, following intravenous, intramuscular and oral doses of ketorolac tromethamine are compared in Table 1. In adults, the extent of bioavailability following administration of the oral and intramuscular forms of ketorolac tromethamine was equal to that following an intravenous bolus.

Table 1: Table of Approximate Average Pharmacokinetic Parameters (Mean±SD) Following
Oral, Intramuscular and Intravenous Doses of Ketorolac Tromethamine
Pharmacokinetic Parameters (units) | Oral† | Intramuscular* |  |  | Intravenous Bolus‡
Pharmacokinetic Parameters (units) | 10 mg | 15 mg | 30 mg | 60 mg | 15 mg | 30 mg
Bioavailability (extent) | 100%
Tmax^1(min) | 44±34 | 33±21** | 44±29 | 33±21** | 1.1±0.7** | 2.9±1.8
Cmax^2(mcg/mL) [Single-dose] | 0.87±0.22 | 1.14±0.32** | 2.42±0.68 | 4.55±1.27** | 2.47±0.51** | 4.65±0.96
Cmax(mcg/mL) [steady state qid] | 1.05±0.26** | 1.56±0.44** | 3.11±0.87** | N/A†† | 3.09±1.17** | 6.85±2.61
Cmin^3(mcg/mL) [steady state qid] | 0.29±0.07** | 0.47±0.13** | 0.93±0.26** | N/A | 0.61±0.21** | 1.04±0.35
Cavg^4(mcg/mL) [steady state qid] | 0.59±0.2** | 0.94±0.29** | 1.88±0.59** | N/A | 1.09±0.3** | 2.17±0.59
Vβ^5(L/kg) | ——————0.175±0.039—————— |  |  |  | 0.210±0.044

% Dose metabolized=<50 | % Dose excreted in feces=6
% Dose excreted in urine=91 | % Plasma protein binding=99 | ^1Time-to-peak plasma concentration
†Derived from oral pharmacokinetic studies in 77 normal fasted volunteers |  | ^2Peak plasma concentration
*Derived from intramuscular pharmacokinetic studies in 54 normal volunteers |  | ^3Trough plasma concentration
‡Derived from intravenous pharmacokinetic studies in 24 normal volunteers |  | ^4Average plasma concentration
††Not applicable because 60 mg is only recommended as a single dose |  | ^5Volume of distribution
**Mean value was simulated from observed plasma concentration data and standard deviation was simulated from percent coefficient of variation for observed Cmaxand Tmaxdata

Linear Kinetics
In adults, following administration of single oral, intramuscular or intravenous doses of ketorolac tromethamine in the recommended dosage ranges, the clearance of the racemate does not change. This implies that the pharmacokinetics of ketorolac tromethamine in adults, following single or multiple intramuscular, intravenous or recommended oral doses of ketorolac tromethamine, are linear. At the higher recommended doses, there is a proportional increase in the concentrations of free and bound racemate.
Distribution
The mean apparent volume (Vβ) of ketorolac tromethamine following complete distribution was approximately 13 liters. This parameter was determined from single-dose data. The ketorolac tromethamine racemate has been shown to be highly protein bound (99%). Nevertheless, plasma concentrations as high as 10 mcg/mL will only occupy approximately 5% of the albumin binding sites. Thus, the unbound fraction for each enantiomer will be constant over the therapeutic range. A decrease in serum albumin, however, will result in increased free drug concentrations.
Ketorolac tromethamine is excreted in human milk (see PRECAUTIONS – Nursing Mothers).
Metabolism
Ketorolac tromethamine is largely metabolized in the liver. The metabolic products are hydroxylated and conjugated forms of the parent drug. The products of metabolism, and some unchanged drug, are excreted in the urine.
Excretion
The principal route of elimination of ketorolac and its metabolites is renal. About 92% of a given dose is found in the urine, approximately 40% as metabolites and 60% as unchanged ketorolac. Approximately 6% of a dose is excreted in the feces. A single-dose study with 10 mg ketorolac tromethamine (n=9) demonstrated that the S-enantiomer is cleared approximately two times faster than the R-enantiomer and that the clearance was independent of the route of administration. This means that the ratio of S/R plasma concentrations decreases with time after each dose. There is little or no inversion of the R- to S- form in humans. The clearance of the racemate in normal subjects, elderly individuals and in hepatically and renally impaired patients is outlined in Table 2 (see CLINICAL PHARMACOLOGY – Kinetics in Special Populations).
The half-life of the ketorolac tromethamine S-enantiomer was approximately 2.5 hours (SD ± 0.4) compared with 5 hours (SD ± 1.7) for the R-enantiomer. In other studies, the half-life for the racemate has been reported to lie within the range of 5 to 6 hours.
Accumulation
Ketorolac tromethamine administered as an intravenous bolus, every 6 hours, for 5 days, to healthy subjects (n = 13), showed no significant difference in Cmaxon Day 1 and Day 5. Trough levels averaged 0.29 mcg/mL (SD ± 0.13) on Day 1 and 0.55 mcg/mL (SD ± 0.23) on Day 6. Steady state was approached after the fourth dose.
Accumulation of ketorolac tromethamine has not been studied in special populations (geriatric, pediatric, renal failure patients, or hepatic disease patients).
Kinetics in Special Populations
Geriatric Patients
Based on single-dose data only, the half-life of the ketorolac tromethamine racemate increased from 5 to 7 hours in the elderly (65 to 78 years) compared with young healthy volunteers (24 to 35 years) (see Table 2). There was little difference in the Cmax for the two groups (elderly, 2.52 mcg/mL ± 0.77; young, 2.99 mcg/mL ± 1.03) (see PRECAUTIONS – Geriatric Use).
Pediatric Patients
Limited information is available regarding the pharmacokinetics of dosing of ketorolac tromethamine in the pediatric population. Following a single intravenous bolus dose of 0.5 mg/kg in 10 children 4 to 8 years old, the half-life was 5.8 ± 1.6 hours, the average clearance was 0.042 ± 0.01 L/hr/kg, the volume of distribution during the terminal phase (Vβ) was 0.34 ± 0.12 L/kg and the volume of distribution at steady state (Vss) was 0.26 ± 0.08 L/kg. The volume of distribution and clearance of ketorolac in pediatric patients was higher than those observed in adult subjects (see Table 1). There are no pharmacokinetic data available for administration of ketorolac tromethamine by the intramuscular route in pediatric patients.
Renal Insufficiency
Based on single-dose data only, the mean half-life of ketorolac tromethamine in renally impaired patients is between 6 and 19 hours and is dependent on the extent of the impairment. There is poor correlation between creatinine clearance and total ketorolac tromethamine clearance in the elderly and populations with renal impairment (r = 0.5).
In patients with renal disease, the AUC∞ of each enantiomer increased by approximately 100% compared with healthy volunteers. The volume of distribution doubles for the S-enantiomer and increases by 1/5th for the R-enantiomer. The increase in volume of distribution of ketorolac tromethamine implies an increase in unbound fraction.
The AUC∞-ratio of the ketorolac tromethamine enantiomers in healthy subjects and patients remained similar, indicating there was no selective excretion of either enantiomer in patients compared to healthy subjects (see WARNINGS – Renal Effects).
Hepatic Insufficiency
There was no significant difference in estimates of half-life, AUC∞ and Cmaxin 7 patients with liver disease compared to healthy volunteers (see PRECAUTIONS – Hepatic Effectsand Table 2).
Race
Pharmacokinetic differences due to race have not been identified.

Table 2: The Influence of Age, Liver and Kidney Function, on the Clearance and
Terminal Half-life of Ketorolac Tromethamine (Intramuscular^1and Oral^2) in Adult Populations
 | Total Clearance [in L/h/kg]^3 |  | Terminal Half-life [in hours]
Type of Subjects | Intramuscular Mean (range) | Oral Mean (range) | Intramuscular Mean (range) | Oral Mean (range)
Normal Subjects Intramuscular (n = 54) mean age = 32, range = 18-60 Oral (n = 77) mean age = 32, range = 20-60 | 0.023 (0.010-0.046) | 0.025 (0.013-0.050) | 5.3 (3.5-9.2) | 5.3 (2.4-9)
Healthy Elderly Subjects Intramuscular (n = 13), Oral (n = 12) mean age = 72, range = 65-78 | 0.019 (0.013-0.034) | 0.024 (0.018-0.034) | 7 (4.7-8.6) | 6.1 (4.3-7.6)
Patients with Hepatic Dysfunction Intramuscular and Oral (n = 7) mean age = 51, range = 43-64 | 0.029 (0.013-0.066) | 0.033 (0.019-0.051) | 5.4 (2.2-6.9) | 4.5 (1.6-7.6)
Patients with Renal Impairment Intramuscular (n = 25), Oral (n = 9) serum creatinine = 1.9-5.0 mg/dL, mean age (Intramuscular) = 54, range = 35-71 mean age (Oral) = 57, range = 39-70 | 0.015 (0.005-0.043) | 0.016 (0.007-0.052) | 10.3 (5.9-19.2) | 10.8 (3.4-18.9)
Renal Dialysis Patients Intramuscular and Oral (n = 9) mean age = 40, range = 27-63 | 0.016 (0.003-0.036) | - | 13.6 (8.0-39.1) | -

^1Estimated from 30 mg single intramuscular doses of ketorolac tromethamine
^2Estimated from 10 mg single oral doses of ketorolac tromethamine
^3Liters/hour/kilogram
Intravenous-Administration:In normal subjects (n=37), the total clearance of 30 mg intravenous-administered ketorolac tromethamine was 0.030 (0.017 to 0.051) L/h/kg. The terminal half-life was 5.6 (4.0 to 7.9) hours. (see Kinetics in Special Populationsfor use of intravenous dosing of ketorolac tromethamine in pediatric patients.)

CLINICAL STUDIES

Adult Patients

In a postoperative study, where all patients received morphine by a PCA device, patients treated with ketorolac tromethamine intravenous as fixed intermittent boluses (e.g., 30 mg initial dose followed by 15 mg every 3 hours), required significantly less morphine (26%) than the placebo group. Analgesia was significantly superior, at various postdosing pain assessment times, in the patients receiving ketorolac tromethamine intravenous plus PCA morphine as compared to patients receiving PCA-administered morphine alone.

INDICATIONS AND USAGE

Carefully consider the potential benefits and risks of ketorolac tromethamine and other treatment options before deciding to use ketorolac. Use the lowest effective dose for the shortest duration consistent with individual patient treatment goals (see WARNINGS).
Acute Pain in Adult Patients
Ketorolac tromethamine is indicated for the short-term (≤5 days) management of moderately severe acute pain that requires analgesia at the opioid level, usually in a postoperative setting. Therapy should always be initiated with intravenous or intramuscular dosing of ketorolac tromethamine, and oral ketorolac tromethamine is to be used only as continuation treatment, if necessary.
The total combined duration of use of ketorolac tromethamine injection and oral ketorolac tromethamine is not to exceed 5 days of use because of the potential of increasing the frequency and severity of adverse reactions associated with the recommended doses (see WARNINGS, PRECAUTIONS, DOSAGE AND ADMINISTRATION, and ADVERSE REACTIONS). Patients should be switched to alternative analgesics as soon as possible, but ketorolac tromethamine therapy is not to exceed 5 days.

CONTRAINDICATIONS

(see also Boxed WARNING)
Ketorolac tromethamine is contraindicated in patients with previously demonstrated hypersensitivity to ketorolac tromethamine.
Ketorolac tromethamine is contraindicated in patients with active peptic ulcer disease, in patients with recent gastrointestinal bleeding or perforation and in patients with a history of peptic ulcer disease or gastrointestinal bleeding.
Ketorolac tromethamine should not be given to patients who have experienced asthma, urticaria, or allergic-type reactions after taking aspirin or other NSAIDs. Severe, rarely fatal, anaphylactic-like reactions to NSAIDs have been reported in such patients (see WARNINGS

– Anaphylactoid Reactions, and PRECAUTIONS – Pre-existing Asthma).

Ketorolac tromethamine is contraindicated as prophylactic analgesic before any major surgery.
Ketorolac tromethamine is contraindicated in the setting of coronary artery bypass graft (CABG) surgery (see WARNINGS).
Ketorolac tromethamine is contraindicated in patients with advanced renal impairment or in patients at risk for renal failure due to volume depletion (see WARNINGSfor correction of volume depletion).
Ketorolac tromethamine is contraindicated in labor and delivery because, through its prostaglandin synthesis inhibitory effect, it may adversely affect fetal circulation and inhibit uterine musculature, thus increasing the risk of uterine hemorrhage.
Ketorolac tromethamine inhibits platelet function and is, therefore, contraindicated in patients with suspected or confirmed cerebrovascular bleeding, hemorrhagic diathesis, incomplete hemostasis and those at high risk of bleeding (see WARNINGSand PRECAUTIONS).
Ketorolac tromethamine is contraindicated in patients currently receiving aspirin or NSAIDs because of the cumulative risks of inducing serious NSAID-related adverse events.
The concomitant use of ketorolac tromethamine and probenecid is contraindicated.
The concomitant use of ketorolac tromethamine and pentoxifylline is contraindicated.
Ketorolac tromethamine injection is contraindicated for neuraxial (epidural or intrathecal) administration due to its alcohol content.

WARNINGS

(see also Boxed WARNING)
The total combined duration of use of oral ketorolac tromethamine and intravenous or intramuscular dosing of ketorolac tromethamine is not to exceed 5 days in adults. Ketorolac tromethamine is not indicated for use in pediatric patients.
The most serious risks associated with ketorolac tromethamine are:

- Gastrointestinal Effects - Risk of Ulceration, Bleeding and Perforation:Ketorolac tromethamine is contraindicated in patients with previously documented peptic ulcers and/or gastrointestinal (GI) bleeding. Ketorolac tromethamine can cause serious GI adverse events including bleeding, ulceration and perforation, of the stomach, small intestine, or large intestine, which can be fatal. These serious adverse events can occur at any time, with or without warning symptoms, in patients treated with ketorolac tromethamine.

Only one in five patients who develop a serious upper GI adverse event on NSAID therapy is symptomatic. Minor upper gastrointestinal problems, such as dyspepsia, are common and may also occur at any time during NSAID therapy.
The incidence and severity of gastrointestinal complications increases with increasing dose of, and duration of treatment with ketorolac tromethamine. Do not use ketorolac tromethamine for more than five days.
However, even short-term therapy is not without risk. In addition to past history of ulcer disease, other factors that increase the risk for GI bleeding in patients treated with NSAIDs include concomitant use of oral corticosteroids, or anticoagulants, longer duration of NSAID therapy, smoking, use of alcohol, older age, and poor general health status. Most spontaneous reports of fatal GI events are in elderly or debilitated patients and therefore, special care should be taken in treating this population.
To minimize the potential risk for an adverse GI event, the lowest effective dose should be used for the shortest possible duration.Patients and physicians should remain alert for signs and symptoms of GI ulceration and bleeding during NSAID therapy and promptly initiate additional evaluation and treatment if a serious GI adverse event is suspected. This should include discontinuation of ketorolac tromethamine until a serious GI adverse event is ruled out. For high risk patients, alternate therapies that do not involve NSAIDs should be considered.
NSAIDs should be given with care to patients with a history of inflammatory bowel disease (ulcerative colitis, Crohn’s disease) as their condition may be exacerbated.
Hemorrhage
Because prostaglandins play an important role in hemostasis and NSAIDs affect platelet aggregation as well, use of ketorolac tromethamine in patients who have coagulation disorders should be undertaken very cautiously, and those patients should be carefully monitored. Patients on therapeutic doses of anticoagulants (e.g., heparin or dicumarol derivatives) have an increased risk of bleeding complications if given ketorolac tromethamine concurrently; therefore, physicians should administer such concomitant therapy only extremely cautiously. The concurrent use of ketorolac tromethamine and therapy that affects hemostasis, including prophylactic low-dose heparin (2500 to 5000 units every 12 hours), warfarin and dextrans have not been studied extensively, but may also be associated with an increased risk of bleeding. Until data from such studies are available, physicians should carefully weigh the benefits against the risks, and use such concomitant therapy in these patients only extremely cautiously. Patients receiving therapy that affects hemostasis should be monitored closely.
In postmarketing experience, postoperative hematomas and other signs of wound bleeding have been reported in association with the peri-operative use of intravenous or intramuscular dosing of ketorolac tromethamine. Therefore, peri-operative use of ketorolac tromethamine should be avoided and postoperative use be undertaken with caution when hemostasis is critical (see PRECAUTIONS).
Renal Effects
Long-term administration of NSAIDs has resulted in renal papillary necrosis and other renal injury. Renal toxicity has also been seen in patients in whom renal prostaglandins have a compensatory role in the maintenance of renal perfusion. In these patients, administration of a NSAID may cause a dose-dependent reduction in prostaglandin formation and, secondarily, in renal blood flow, which may precipitate overt renal decompensation. Patients at greatest risk of this reaction are those with impaired renal function, heart failure, liver dysfunction, those taking diuretics and ACE inhibitors, and the elderly. Discontinuation of NSAID therapy is usually followed by recovery to the pretreatment state.
Ketorolac tromethamine and its metabolites are eliminated primarily by the kidneys, which, in patients with reduced creatinine clearance, will result in diminished clearance of the drug (see CLINICAL PHARMACOLOGY). Therefore, ketorolac tromethamine should be used with caution in patients with impaired renal function (see DOSAGE AND ADMINISTRATION) and such patients should be followed closely. With the use of ketorolac tromethamine, there have been reports of acute renal failure, interstitial nephritis and nephrotic syndrome.
Impaired Renal Function
Ketorolac tromethamine is contraindicated in patients with serum creatinine concentrations indicating advanced renal impairment (see CONTRAINDICATIONS). Ketorolac tromethamine should be used with caution in patients with impaired renal function or a history of kidney disease because it is a potent inhibitor of prostaglandin synthesis. Because patients with underlying renal insufficiency are at increased risk of developing acute renal decompensation or failure, the risks and benefits should be assessed prior to giving ketorolac tromethamine to these patients.
Anaphylactoid Reactions
As with other NSAIDs, anaphylactoid reactions may occur in patients without known prior exposure to ketorolac tromethamine. Ketorolac tromethamine should not be given to patients with the aspirin triad. This symptom complex typically occurs in asthmatic patients who experience rhinitis with or without nasal polyps, or who exhibit severe, potentially fatal bronchospasm after taking aspirin or other NSAIDs (see CONTRAINDICATIONSand PRECAUTIONS–Pre-existing Asthma). Emergency help should be sought in cases where an anaphylactoid reaction occurs.
Cardiovascular Effects
Cardiovascular Thrombotic Events
Clinical trials of several COX-2 selective and nonselective NSAIDs of up to three years duration have shown an increased risk of serious cardiovascular (CV) thrombotic events, including myocardial infarction (MI) and stroke, which can be fatal. Based on available data, it is unclear that the risk for CV thrombotic events is similar for all NSAIDs. The relative increase in serious CV thrombotic events over baseline conferred by NSAID use appears to be similar in those with and without known CV disease or risk factors for CV disease. However, patients with known CV disease or risk factors had a higher absolute incidence of excess serious CV thrombotic events, due to their increased baseline rate. Some observational studies found that this increased risk of serious CV thrombotic events began as early as the first few weeks of treatment. The increase in CV thrombotic risk has been observed most consistently at higher doses.

To minimize the potential risk for an adverse CV event in NSAID-treated patients, use the lowest effective dose for the shortest duration possible. Physicians and patients should remain alert for the development of such events, throughout the entire treatment course, even in the absence of previous CV symptoms. Patients should be informed about the symptoms of serious CV events and the steps to take if they occur.

There is no consistent evidence that concurrent use of aspirin mitigates the increased risk of serious CV thrombotic events associated with NSAID use. The concurrent use of aspirin and an NSAID, such as ketorolac tromethamine, increases the risk of serious gastrointestinal (GI) events (see WARNINGS).

Status Post Coronary Artery Bypass Graft (CABG) Surgery

Two large, controlled clinical trials of a COX-2 selective NSAID for the treatment of pain in the first 10 to 14 days following CABG surgery found an increased incidence of myocardial infarction and stroke. NSAIDs are contraindicated in the setting of CABG surgery (see CONTRAINDICATIONS).

Post-MI Patients

Observational studies conducted in the Danish National Registry have demonstrated that patients treated with NSAIDs in the post-MI period were at increased risk of reinfarction, CV-related death, and all-cause mortality beginning in the first week of treatment. In this same cohort, the incidence of death in the first year post MI was 20 per 100 person years in NSAID-treated patients compared to 12 per 100 person years in non-NSAID exposed patients. Although the absolute rate of death declined somewhat after the first year post-MI, the increased relative risk of death in NSAID users persisted over at least the next four years follow-up.

Avoid the use of ketorolac tromethamine in patients with a recent MI unless the benefits are expected to outweigh the risk of recurrent CV thrombotic events. If ketorolac tromethamine is used in patients with a recent MI, monitor patients for signs of cardiac ischemia.

Hypertension
NSAIDs, including ketorolac tromethamine, can lead to onset of new hypertension or worsening of pre-existing hypertension, either of which may contribute to the increased incidence of CV events. Patients taking thiazides or loop diuretics may have impaired response to these therapies when taking NSAIDs. NSAIDs, including ketorolac tromethamine, should be used with caution in patients with hypertension. Blood pressure (BP) should be monitored closely during the initiation of NSAID treatment and throughout the course of therapy.
Heart Failure and Edema
The Coxib and traditional NSAID Trialists’ Collaboration meta-analysis of randomized controlled trials demonstrated an approximately two-fold increase in hospitalizations for heart failure in COX-2 selective-treated patients and nonselective NSAID-treated patients compared to placebo-treated patients. In a Danish National Registry study of patients with heart failure, NSAID use increased the risk of MI, hospitalization for heart failure, and death.
Additionally, fluid retention and edema have been observed in some patients treated with NSAIDs. Use of ketorolac tromethamine may blunt the CV effects of several therapeutic agents used to treat these medical conditions (e.g., diuretics, ACE inhibitors, or angiotensin receptor blockers (ARBs) (see PRECAUTIONS – Drug Interactions).
Avoid the use of ketorolac tromethamine in patients with severe heart failure unless the benefits are expected to outweigh the risk of worsening heart failure. If ketorolac tromethamine is used in patients with severe heart failure, monitor patients for signs of worsening heart failure.
Skin Reactions
NSAIDs, including ketorolac tromethamine, can cause serious skin adverse events such as exfoliative dermatitis, Stevens-Johnson Syndrome (SJS), and toxic epidermal necrolysis (TEN), which can be fatal. These serious events may occur without warning. Patients should be informed about the signs and symptoms of serious skin manifestations and use of the drug should be discontinued at the first appearance of skin rash or any other sign of hypersensitivity.

Drug Reaction with Eosinophilia and Systemic Symptoms (DRESS)

Drug Reaction with Eosinophilia and Systemic Symptoms (DRESS) has been reported in patients taking NSAIDs such as ketorolac tromethamine. Some of these events have been fatal or life-threatening. DRESS typically, although not exclusively, presents with fever, rash, lymphadenopathy, and/or facial swelling. Other clinical manifestations may include hepatitis, nephritis, hematological abnormalities, myocarditis, or myositis. Sometimes symptoms of DRESS may resemble an acute viral infection. Eosinophilia is often present. Because this disorder is variable in its presentation, other organ systems not noted here may be involved. It is important to note that early manifestations of hypersensitivity, such as fever or lymphadenopathy, may be present even though rash is not evident. If such signs or symptoms are present, discontinue ketorolac tromethamine and evaluate the patient immediately.

Fetal Toxicity

Premature Closure of Fetal Ductus Arteriosus:

Avoid use of NSAIDs, including ketorolac tromethamine, in pregnant women at about 30 weeks gestation and later. NSAIDs including ketorolac tromethamine, increase the risk of premature closure of the fetal ductus arteriosus at approximately this gestational age.

Oligohydramnios/Neonatal Renal Impairment:

Use of NSAIDs, including ketorolac tromethamine, at about 20 weeks gestation or later in pregnancy may cause fetal renal dysfunction leading to oligohydramnios and, in some cases, neonatal renal impairment. These adverse outcomes are seen, on average, after days to weeks of treatment, although oligohydramnios has been infrequently reported as soon as 48 hours after NSAID initiation. Oligohydramnios is often, but not always, reversible with treatment discontinuation. Complications of prolonged oligohydramnios may, for example, include limb contractures and delayed lung maturation. In some postmarketing cases of impaired neonatal renal function, invasive procedures such as exchange transfusion or dialysis were required.

If NSAID treatment is necessary between about 20 weeks and 30 weeks gestation, limit ketorolac tromethamine use to the lowest effective dose and shortest duration possible. Consider ultrasound monitoring of amniotic fluid if ketorolac tromethamine treatment extends beyond 48 hours. Discontinue ketorolac tromethamine if oligohydramnios occurs and follow up according to clinical practice (see PRECAUTIONS; Pregnancy).

PRECAUTIONS

General

Ketorolac tromethamine cannot be expected to substitute for corticosteroids or to treat corticosteroid insufficiency. Abrupt discontinuation of corticosteroids may lead to disease exacerbation. Patients on prolonged corticosteroid therapy should have their therapy tapered slowly if a decision is made to discontinue corticosteroids.

The pharmacological activity of ketorolac tromethamine in reducing inflammation may diminish the utility of this diagnostic sign in detecting complications of presumed noninfectious, painful conditions.
Hepatic Effects

Ketorolac tromethamine should be used with caution in patients with impaired hepatic function or a history of liver disease. Borderline elevations of one or more liver tests may occur in up to 15% of patients taking NSAIDs including ketorolac tromethamine. These laboratory abnormalities may progress, may remain unchanged, or may be transient with continuing therapy. Notable elevations of ALT or AST (approximately three or more times the upper limit of normal) have been reported in approximately 1% of patients in clinical trials with NSAIDs. In addition, rare cases of severe hepatic reactions, including jaundice and fatal fulminant hepatitis, liver necrosis and hepatic failure, some of them with fatal outcomes have been reported.

A patient with symptoms and/or signs suggesting liver dysfunction, or in whom an abnormal liver test has occurred, should be evaluated for evidence of the development of a more severe hepatic reaction while on therapy with ketorolac tromethamine. If clinical signs and symptoms consistent with liver disease develop, or if systemic manifestations occur (e.g., eosinophilia, rash, etc.), ketorolac tromethamine should be discontinued.
Hematologic Effects

Anemia is sometimes seen in patients receiving NSAIDs, including ketorolac tromethamine. This may be due to fluid retention, occult or gross GI blood loss, or an incompletely described effect upon erythropoiesis. Patients on long-term treatment with NSAIDs, including ketorolac tromethamine, should have their hemoglobin or hematocrit checked if they exhibit any signs or symptoms of anemia. NSAIDs inhibit platelet aggregation and have been shown to prolong bleeding time in some patients. Unlike aspirin, their effect on platelet function is quantitatively less, of shorter duration, and reversible. Patients receiving ketorolac tromethamine who may be adversely affected by alterations in platelet function, such as those with coagulation disorders or patients receiving anticoagulants, should be carefully monitored.
Pre-existing Asthma

Patients with asthma may have aspirin-sensitive asthma. The use of aspirin in patients with aspirin-sensitive asthma has been associated with severe bronchospasm which can be fatal. Since cross reactivity, including bronchospasm, between aspirin and other nonsteroidal anti-inflammatory drugs has been reported in such aspirin-sensitive patients, ketorolac tromethamine should not be administered to patients with this form of aspirin sensitivity and should be used with caution in patients with pre-existing asthma.

Information for Patients

Ketorolac tromethamine is a potent NSAID and may cause serious side effects such as gastrointestinal bleeding or kidney failure, which may result in hospitalization and even fatal outcome.

Physicians, when prescribing ketorolac tromethamine, should inform their patients or their guardians of the potential risks of ketorolac tromethamine treatment (see Boxed WARNING, WARNINGS, PRECAUTIONS, and ADVERSE REACTIONSsections), instruct patients to seek medical advice if they develop treatment-related adverse events, and advise patients not to give oral ketorolac tromethamine to other family members and to discard any unused drug. Remember that the total combined duration of use of oral ketorolac tromethamine and intravenous or intramuscular dosing of ketorolac tromethamine is not to exceed 5 days in adults. Ketorolac tromethamine is not indicated for use in pediatric patients. Patients should be informed of the following information before initiating therapy with an NSAID and periodically during the course of ongoing therapy. Patients should also be encouraged to read the NSAID Medication Guide that accompanies each prescription dispensed.

1. Advise patients to be alert for the symptoms of cardiovascular thrombotic events, including chest pain, shortness of breath, weakness, or slurring of speech, and to report any of these symptoms to their health care provider immediately (see WARNINGS).

2. Ketorolac tromethamine, like other NSAIDs, can cause GI discomfort and, rarely, serious GI side effects, such as ulcers and bleeding, which may result in hospitalization and even death. Although serious GI tract ulcerations and bleeding can occur without warning symptoms, patients should be alert for the signs and symptoms of ulcerations and bleeding, and should ask for medical advice when observing any indicative sign or symptoms including epigastric pain, dyspepsia, melena, and hematemesis. Patients should be apprised of the importance of this follow-up (see WARNINGS, Gastrointestinal Effects: Risk of Ulceration, Bleeding, and Perforation).

3. Serious Skin Reactions, including DRESS

Advise patients to stop taking ketorolac tromethamine immediately if they develop any type of rash or fever and to contact their healthcare provider as soon as possible (see WARNINGS).

4. Advise patients to be alert for the symptoms of congestive heart failure including shortness of breath, unexplained weight gain, or edema and to contact their healthcare provider if such symptoms occur (see WARNINGS).
5. Patients should be informed of the warning signs and symptoms of hepatotoxicity (e.g., nausea, fatigue, lethargy, pruritus, jaundice, right upper quadrant tenderness, and "flu-like" symptoms). If these occur, patients should be instructed to stop therapy and seek immediate medical therapy.
6. Patients should be informed of the signs of an anaphylactoid reaction (e.g., difficulty breathing, swelling of the face or throat). If these occur, patients should be instructed to seek immediate emergency help (see WARNINGS).
7. Fetal Toxicity

Inform pregnant women to avoid use of ketorolac tromethamine and other NSAIDs starting at 30 weeks gestation because of the risk of the premature closing of the fetal ductus arteriosus. If treatment with ketorolac tromethamine is needed for a pregnant woman between about 20 to 30 weeks gestation, advise her that she may need to be monitored for oligohydramnios, if treatment continues for longer than 48 hours (see WARNINGS; Fetal Toxicity, PRECAUTIONS; Pregnancy).

Laboratory Tests

Because serious GI tract ulcerations and bleeding can occur without warning symptoms, physicians should monitor for signs or symptoms of GI bleeding. Patients on long-term treatment with NSAIDs, should have their CBC and a chemistry profile checked periodically. If clinical signs and symptoms consistent with liver or renal disease develop, systemic manifestations occur (e.g., eosinophilia, rash etc.) or if abnormal liver tests persist or worsen, ketorolac tromethamine should be discontinued.

Drug Interactions

Ketorolac is highly bound to human plasma protein (mean 99.2%). There is no evidence in animal or human studies that ketorolac tromethamine induces or inhibits hepatic enzymes capable of metabolizing itself or other drugs.

Warfarin, Digoxin, Salicylate, and Heparin

The in vitrobinding of warfarinto plasma proteins is only slightly reduced by ketorolac tromethamine (99.5% control vs 99.3%) when ketorolac plasma concentrations reach 5 to 10 mcg/mL. Ketorolac does not alter digoxinprotein binding. In vitrostudies indicate that, at therapeutic concentrations of salicylate(300 mcg/mL), the binding of ketorolac was reduced from approximately 99.2% to 97.5%, representing a potential two-fold increase in unbound ketorolac plasma levels. Therapeutic concentrations of digoxin, warfarin, ibuprofen, naproxen, piroxicam, acetaminophen, phenytoinand tolbutamidedid not alter ketorolac tromethamine protein binding.

In a study involving 12 adult volunteers, oral ketorolac tromethamine was coadministered with a single dose of 25 mg warfarin, causing no significant changes in pharmacokinetics or pharmacodynamics of warfarin. In another study, ketorolac tromethamine dosed intravenous or intramuscular was given with two doses of 5000 U of heparinto 11 healthy volunteers, resulting in a mean template bleeding time of 6 minutes (3.2 to 11.4 min) compared to a mean of 6.0 minutes (3.4 to 7.5 min) for heparin alone and 5.1 minutes (3.5 to 8.5 min) for placebo. Although these results do not indicate a significant interaction between ketorolac tromethamine and warfarin or heparin, the administration of ketorolac tromethamine to patients taking anticoagulants should be done extremely cautiously, and patients should be closely monitored (see WARNINGSand PRECAUTIONS – Hematologic Effects).

The effects of warfarin and NSAIDs, in general, on GI bleeding are synergistic, such that the users of both drugs together have a risk of serious GI bleeding higher than the users of either drug alone.

Aspirin

When ketorolac tromethamine is administered with aspirin, its protein binding is reduced, although the clearance of free ketorolac tromethamine is not altered. The clinical significance of this interaction is not known; however, as with other NSAIDs, concomitant administration of ketorolac tromethamine and aspirin is not generally recommended because of the potential of increased adverse effects.

Diuretics

Clinical studies, as well as postmarketing observations, have shown that ketorolac tromethamine can reduce the natriuretic effect of furosemide and thiazides in some patients. This response has been attributed to inhibition of renal prostaglandin synthesis. During concomitant therapy with NSAIDs, the patient should be observed closely for signs of renal failure (see WARNINGS – Renal Effects), as well as to assure diuretic efficacy.

Probenecid

Concomitant administration of oral ketorolac tromethamine and probenecid resulted in decreased clearance and volume of distribution of ketorolac and significant increases in ketorolac plasma levels (total AUC increased approximately three-fold from 5.4 to 17.8 mcg/h/mL) and terminal half-life increased approximately two-fold from 6.6 to 15.1 hours. Therefore, concomitant use of ketorolac tromethamine and probenecid is contraindicated.

Lithium

NSAIDs have produced an elevation of plasma lithium levels and a reduction in renal lithium clearance. The mean minimum lithium concentration increased 15% and the renal clearance was decreased by approximately 20%. These effects have been attributed to inhibition of renal prostaglandin synthesis by the NSAID. Thus, when NSAIDs and lithium are administered concurrently, subjects should be observed carefully for signs of lithium toxicity.

Methotrexate

NSAIDs have been reported to competitively inhibit methotrexate accumulation in rabbit kidney slices. This may indicate that they could enhance the toxicity of methotrexate. Caution should be used when NSAIDs are administered concomitantly with methotrexate.

ACE Inhibitors/Angiotensin II Receptor Antagonists

Concomitant use of ACE inhibitors and/or angiotensin II receptor antagonistsmay increase the risk of renal impairment, particularly in volume-depleted patients.

Reports suggest that NSAIDs may diminish the antihypertensive effect of ACE inhibitors and/or angiotensin II receptor antagonists. This interaction should be given consideration in patients taking NSAIDs concomitantly with ACE inhibitors and/or angiotensin II receptor antagonists.

Antiepileptic Drugs

Sporadic cases of seizures have been reported during concomitant use of ketorolac tromethamine and antiepileptic drugs (phenytoin, carbamazepine).

Psychoactive Drugs

Hallucinations have been reported when ketorolac tromethamine was used in patients taking psychoactive drugs (fluoxetine, thiothixene, alprazolam).

Pentoxifylline

When ketorolac tromethamine is administered concurrently with pentoxifylline, there is an increased tendency to bleeding.

Nondepolarizing Muscle Relaxants

In postmarketing experience there have been reports of a possible interaction between ketorolac tromethamine intravenous/intramuscular and nondepolarizing muscle relaxantsthat resulted in apnea. The concurrent use of ketorolac tromethamine with muscle relaxants has not been formally studied.

Selective Serotonin Reuptake Inhibitors (SSRIs)

There is an increased risk of gastrointestinal bleeding when selective serotonin reuptake inhibitors(SSRIs) are combined with NSAIDs. Caution should be used when NSAIDs are administered concomitantly with SSRIs.

Carcinogenesis, Mutagenesis, and Impairment of Fertility

An 18-month study in mice with oral doses of ketorolac tromethamine tablets at 2 mg/kg/day (0.9 times the human systemic exposure at the recommended intramuscular or intravenous dose of 30 mg qid, based on area-under-the-plasma-concentration curve [AUC]), and a 24-month study in rats at 5 mg/kg/day (0.5 times the human AUC) showed no evidence of tumorigenicity.

Ketorolac tromethamine was not mutagenic in the Ames test, unscheduled DNA synthesis and repair, and in forward mutation assays. Ketorolac tromethamine did not cause chromosome breakage in the in vivomouse micronucleus assay. At 1590 mcg/mL and at higher concentrations, ketorolac tromethamine increased the incidence of chromosomal aberrations in Chinese hamster ovarian cells.

Impairment of fertility did not occur in male or female rats at oral doses of 9 mg/kg (0.9 times the human AUC) and 16 mg/kg (1.6 times the human AUC) of ketorolac tromethamine, respectively.

Pregnancy

Risk Summary

Use of NSAIDs, including ketorolac tromethamine, can cause premature closure of the fetal ductus arteriosus and fetal renal dysfunction leading to oligohydramnios and, in some cases, neonatal renal impairment. Because of these risks, limit dose and duration of ketorolac tromethamine use between about 20 and 30 weeks of gestation, and avoid ketorolac tromethamine use at about 30 weeks of gestation and later in pregnancy (see WARNINGS; Fetal Toxicity).

Premature Closure of Fetal Ductus Arteriosus:

Use of NSAIDs, including ketorolac tromethamine, at about 30 weeks gestation or later in pregnancy increases the risk of premature closure of the fetal ductus arteriosus.

Oligohydramnios/Neonatal Renal Impairment:

Use of NSAIDs at about 20 weeks gestation or later in pregnancy has been associated with cases of fetal renal dysfunction leading to oligohydramnios, and in some cases, neonatal renal impairment.

Data from observational studies regarding other potential embryofetal risks of NSAID use in women in the first or second trimesters of pregnancy are inconclusive. Reproduction studies have been performed during organogenesis using daily oral doses of ketorolac tromethamine at 3.6 mg/kg (0.37 times the human AUC) in rabbits and at 10 mg/kg (1.0 times the human AUC) in rats. Results of these studies did not reveal evidence of teratogenicity to the fetus. However, animal reproduction studies are not always predictive of human response. Oral doses of ketorolac tromethamine at 1.5 mg/kg (0.14 times the human AUC), administered after gestation Day 17, caused dystocia and higher pup mortality in rats. Based on animal data, prostaglandins have been shown to have an important role in endometrial vascular permeability, blastocyst implantation, and decidualization. In animal studies, administration of prostaglandin synthesis inhibitors such as ketorolac tromethamine, resulted in increased pre- and post-implantation loss. Prostaglandins also have been shown to have an important role in fetal kidney development. In published animal studies, prostaglandin synthesis inhibitors have been reported to impair kidney development when administered at clinically relevant doses.

The estimated background risk of major birth defects and miscarriage for the indicated population(s) is unknown. All pregnancies have a background risk of birth defect, loss, or other adverse outcomes. In the U.S. general population, the estimated background risk of major birth defects and miscarriage in clinically recognized pregnancies is 2 to 4% and 15 to 20%, respectively.

Clinical Considerations

Fetal/Neonatal Adverse Reactions

Premature Closure of Fetal Ductus Arteriosus:

Avoid use of NSAIDs in women at about 30 weeks gestation and later in pregnancy, because NSAIDs, including ketorolac tromethamine, can cause premature closure of the fetal ductus arteriosus (see WARNINGS; Fetal Toxicity).

Oligohydramnios/Neonatal Renal Impairment:

If an NSAID is necessary at about 20 weeks gestation or later in pregnancy, limit the use to the lowest effective dose and shortest duration possible. If ketorolac tromethamine treatment extends beyond 48 hours, consider monitoring with ultrasound for oligohydramnios. If oligohydramnios occurs, discontinue ketorolac tromethamine and follow up according to clinical practice (see WARNINGS; Fetal Toxicity).

Data

Human Data

There are no adequate and well-controlled studies of ketorolac tromethamine in pregnant women. Ketorolac tromethamine should be used during pregnancy only if the potential benefit justifies the potential risk to the fetus.

Premature Closure of Fetal Ductus Arteriosus

Published literature reports that the use of NSAIDs at about 30 weeks of gestation and later in pregnancy may cause premature closure of the fetal ductus arteriosus.

Oligohydramnios/Neonatal Renal Impairment

Published studies and postmarketing reports describe maternal NSAID use at about 20 weeks gestation or later in pregnancy associated with fetal renal dysfunction leading to oligohydramnios, and in some cases, neonatal renal impairment. These adverse outcomes are seen, on average, after days to weeks of treatment, although oligohydramnios has been infrequently reported as soon as 48 hours after NSAID initiation. In many cases, but not all, the decrease in amniotic fluid was transient and reversible with cessation of the drug. There have been a limited number of case reports of maternal NSAID use and neonatal renal dysfunction without oligohydramnios, some of which were irreversible. Some cases of neonatal renal dysfunction required treatment with invasive procedures, such as exchange transfusion or dialysis.

Methodological limitations of these postmarketing studies and reports include lack of a control group; limited information regarding dose, duration, and timing of drug exposure; and concomitant use of other medications. These limitations preclude establishing a reliable estimate of the risk of adverse fetal and neonatal outcomes with maternal NSAID use. Because the published safety data on neonatal outcomes involved mostly preterm infants, the generalizability of certain reported risks to the full-term infant exposed to NSAIDs through maternal use is uncertain.

Labor and Delivery

The use of ketorolac tromethamine is contraindicated in labor and delivery because, through its prostaglandin synthesis inhibitory effect, it may adversely affect fetal circulation and inhibit uterine contractions, thus increasing the risk of uterine hemorrhage (see CONTRAINDICATIONS).

Effects on Fertility

The use of ketorolac tromethamine, as with any drug known to inhibit cyclooxygenase/ prostaglandin synthesis, may impair fertility and is not recommended in women attempting to conceive. In women who have difficulty conceiving or are undergoing investigation of infertility, withdrawal of ketorolac tromethamine should be considered.

Nursing Mothers

Limited data from one published study that included 10 breastfeeding women 2-6 days postpartum showed low levels of ketorolac in breast milk and were undetectable (less than 5 ng/mL) in 4 of the patients. After a single administration of 10 mg of ketorolac tromethamine, the maximum milk concentration observed was 7.3 ng/mL, and the maximum milk-to-plasma ratio was 0.037. After 1 day of dosing (10 mg every 6 hours), the maximum milk concentration was 7.9 ng/mL, and the maximum milk-to-plasma ratio was 0.025. Assuming a daily intake of 400 to 1,000 mL of human milk per day and a maternal body weight of 60 kg, the calculated maximum daily infant exposure was 0.00263 mg/kg/day, which is 0.4% of the maternal weight-adjusted dose.
Exercise caution when ketorolac is administered to a nursing woman. Available information has not shown any specific adverse events in nursing infants; however, instruct patients to contact their infant's healthcare provider if they note any adverse events.

Pediatric Use

Ketorolac tromethamine is not indicated for use in pediatric patients. The safety and effectiveness of ketorolac tromethamine in pediatric patients below the age of 17 years have not been established.

Geriatric Use

(≥ 65 Years of Age)
Because ketorolac tromethamine may be cleared more slowly by the elderly (see CLINICAL PHARMACOLOGY) who are also more sensitive to the dose-related adverse effects of NSAIDs (see WARNINGS - Gastrointestinal Effects - Risk of Ulceration, Bleeding, and Perforation), extreme caution and reduced dosages (see DOSAGE AND ADMINISTRATION) and careful clinical monitoring must be used when treating the elderly with ketorolac tromethamine .

ADVERSE REACTIONS

Adverse reaction rates increase with higher doses of ketorolac tromethamine. Practitioners should be alert for the severe complications of treatment with ketorolac tromethamine, such as G.I. ulceration, bleeding and perforation, postoperative bleeding, acute renal failure, anaphylactic and anaphylactoid reactions and liver failure (see Boxed WARNING, WARNINGS, PRECAUTIONS, and DOSAGE AND ADMINISTRATION). These NSAID-related complications can be serious in certain patients for whom ketorolac tromethamine is indicated, especially when the drug is used inappropriately.
In patients taking ketorolac tromethamine or other NSAIDs in clinical trials, the most frequently reported adverse experiences in approximately 1% to 10% of patients are:

Gastrointestinal (GI) experiences including:
abdominal pain | constipation/diarrhea | dyspepsia
flatulence | GI fullness | GI ulcers (gastric/duodenal)
gross bleeding/perforation | heartburn | nausea*
stomatitis | vomiting
Other experiences:
abnormal renal function | anemia | dizziness
drowsiness | edema | elevated liver enzymes
headaches* | hypertension | increased bleeding time
injection site pain | pruritus | purpura
rashes | tinnitus | sweating

*Incidence greater than 10%

Additional adverse experiences reported occasionally (<1% in patients taking ketorolac tromethamine or other NSAIDs in clinical trials) include:

Body as a Whole:fever, infections, sepsis

Cardiovascular:congestive heart failure, palpitation, pallor, tachycardia, syncope

Dermatologic:alopecia, photosensitivity, urticaria

Gastrointestinal:anorexia, dry mouth, eructation, esophagitis, excessive thirst, gastritis, glossitis, hematemesis, hepatitis, increased appetite, jaundice, melena, rectal bleeding

Hemic and Lymphatic:ecchymosis, eosinophilia, epistaxis, leukopenia, thrombocytopenia

Metabolic and Nutritional:weight change
Nervous System:abnormal dreams, abnormal thinking, anxiety, asthenia, confusion, depression, euphoria, extrapyramidal symptoms, hallucinations, hyperkinesis, inability to concentrate, insomnia, nervousness, paresthesia, somnolence, stupor, tremors, vertigo, malaise

Reproductive, female:infertility

Respiratory:asthma, cough, dyspnea, pulmonary edema, rhinitis

Special Senses:abnormal taste, abnormal vision, blurred vision, hearing loss

Urogenital:cystitis, dysuria, hematuria, increased urinary frequency, interstitial nephritis, oliguria/polyuria, proteinuria, renal failure, urinary retention
Other rarely observed reactions (reported from postmarketing experience in patients taking ketorolactromethamine or other NSAIDs) are:

Body as a Whole:angioedema, death, hypersensitivity reactions such as anaphylaxis, anaphylactoid reaction, laryngeal edema, tongue edema (see WARNINGS), myalgia
Cardiovascular:arrhythmia, bradycardia, chest pain, flushing, hypotension, myocardial infarction, vasculitis
Dermatologic:exfoliative dermatitis, erythema multiforme, Lyell's syndrome, bullous reactions including Stevens-Johnson syndrome and toxic epidermal necrolysis

Gastrointestinal:acute pancreatitis, liver failure, ulcerative stomatitis, exacerbation of inflammatory bowel disease (ulcerative colitis, Crohn’s disease)

Hemic and Lymphatic:agranulocytosis, aplastic anemia, hemolytic anemia, lymphadenopathy, pancytopenia, post operative wound hemorrhage (rarely requiring blood transfusion — see Boxed WARNING, WARNINGS, and PRECAUTIONS)

Metabolic and Nutritional:hyperglycemia, hyperkalemia, hyponatremia

Nervous System:aseptic meningitis, convulsions, coma, psychosis

Respiratory:bronchospasm, respiratory depression, pneumonia

Special Senses:conjunctivitis

Urogenital:flank pain with or without hematuria and/or azotemia, hemolytic uremic syndrome
Postmarketing Surveillance Study

A large postmarketing observational, nonrandomized study, involving approximately 10,000 patients receiving ketorolac tromethamine, demonstrated that the risk of clinically serious gastrointestinal (GI) bleeding was dose-dependent (see Tables 3Aand 3B). This was particularly true in elderly patients who received an average daily dose greater than 60 mg/day of ketorolac tromethamine (see Table 3A).

Table 3: Incidence of Clinically Serious G.I. Bleeding as Related to Age, Total Daily Dose, and History of G.I. Perforation, Ulcer, Bleeding (PUB) after up to 5 Days of Treatment with Ketorolac Tromethamine Injection
A. Adult Patients without History of PUB
Age of Patients | Total Daily Dose of Ketorolac Tromethamine Injection
Age of Patients | ≤60 mg | >60 to 90 mg | >90 to 120 mg | >120 mg
<65 years of age | 0.4% | 0.4% | 0.9% | 4.6%
≥65 years of age | 1.2% | 2.8% | 2.2% | 7.7%
B. Adult Patients with History of PUB
Age of Patients | Total Daily Dose of Ketorolac Tromethamine Injection
Age of Patients | ≤60 mg | >60 to 90 mg | >90 to 120 mg | >120 mg
<65 years of age | 2.1% | 4.6% | 7.8% | 15.4%
≥65 years of age | 4.7% | 3.7% | 2.8% | 25.0%

To report SUSPECTED ADVERSE REACTIONS, contact Fosun Pharma USA Inc. at 1-866-611-3762 or FDA at 1-800-FDA-1088 or www.fda.gov/medwatch.

OVERDOSAGE

Symptoms and Signs
Symptoms following acute NSAIDs overdoses are usually limited to lethargy, drowsiness, nausea, vomiting, and epigastric pain, which are generally reversible with supportive care. Gastrointestinal bleeding can occur. Hypertension, acute renal failure, respiratory depression and coma may occur, but are rare. Anaphylactoid reactions have been reported with therapeutic ingestion of NSAIDs, and may occur following an overdose.
Treatment
Patients should be managed by symptomatic and supportive care following a NSAIDs overdose. There are no specific antidotes. Forced diuresis, alkalization of urine, hemodialysis or hemoperfusion may not be useful due to high protein binding.

Single overdoses of ketorolac tromethamine have been variously associated with abdominal pain, nausea, vomiting, hyperventilation, peptic ulcers and/or erosive gastritis and renal dysfunction which have resolved after discontinuation of dosing.

DOSAGE AND ADMINISTRATION

Carefully consider the potential benefits and risks of ketorolac tromethamine and other treatment options before deciding to use ketorolac tromethamine. Use the lowest effective dose for the shortest duration consistent with individual patient treatment goals. In adults, the combined duration of use of intravenous or intramuscular dosing of ketorolac tromethamine and oral ketorolac tromethamine is not to exceed 5 days. In adults, the use of oral ketorolac tromethamine is only indicated as continuation therapy to intravenous or intramuscular dosing of ketorolac tromethamine. See package insert for ketorolac tromethamine tablets for transition from intravenous or intramuscular dosing of ketorolac tromethamine (single- or multiple-dose) to multiple-dose oral ketorolac tromethamine.
Note: Oral formulationshould notbe given as an initial dose.

Use minimum effective dosefor the individual patient.

Total duration of treatment in adult patients:the combined duration of use of intravenous or intramuscular dosing of ketorolac tromethamine and oral ketorolac tromethamine is not to exceed 5 days.

KETOROLAC TROMETHAMINE INJECTION

Ketorolac tromethamine injection may be used as a single or multiple dose on a regular or “as needed” schedule for the management of moderately severe, acute pain that requires analgesia at the opioid level, usually in a postoperative setting. Hypovolemia should be corrected prior to the administration of ketorolac tromethamine (see WARNINGS - Renal Effects). Patients should be switched to alternative analgesics as soon as possible, but ketorolac tromethamine therapy is not to exceed 5 days.
When administering ketorolac tromethamine injection, the intravenous bolus must be given over no less than 15 seconds. The intramuscular administration should be given slowly and deeply into the muscle. The analgesic effect begins in ~30 minutes with maximum effect in 1 to 2 hours after dosing intravenous or intramuscular. Duration of analgesic effect is usually 4 to 6 hours.
Single-Dose Treatment: The following regimen should be limited to single administration use only
Intramuscular Dosing
• Patients <65 years of age: One dose of 60 mg.
• Patients ≥65 years of age, renally impaired and/or less than 50 kg (110 lbs) of body weight:

One dose of 30 mg.
Intravenous Dosing
• Patients <65 years of age: One dose of 30 mg.
•Patients ≥65 years of age, renally impaired and/or less than 50 kg (110 lbs) of body weight:One dose of 15 mg.
Multiple-Dose Treatment (Intravenous or Intramuscular)
• Patients <65 years of age: The recommended dose is 30 mg ketorolac tromethamine injection every 6 hours. The maximum daily dose for these populations should
not exceed 120 mg.
• For patients ≥65 years of age, renally impaired patients (see WARNINGS), and patients less than 50 kg (110 lbs): The recommended dose is 15 mg ketorolac tromethamine injection every 6 hours. The maximum daily dose for these populations should not exceed 60 mg.

For breakthrough pain, do not increase the dose or the frequency of ketorolac tromethamine. Consideration should be given to supplementing these regimens with low doses of opioids "as needed" unless otherwise contraindicated.
Pharmaceutical Information for Ketorolac Tromethamine Injection

Ketorolac tromethamine injection should not be mixed in a small volume (e.g., in a syringe) with morphine sulfate, meperidine hydrochloride, promethazine hydrochloride or hydroxyzine hydrochloride; this will result in precipitation of ketorolac from solution.

NOTE:Parenteral drug products should be inspected visually for particulate matter and discoloration prior to administration, whenever solution and container permit.

HOW SUPPLIED

Ketorolac Tromethamine Injection, USP is supplied as follows:

NDC Number | Ketorolac Tromethamine Injection USP | Package Factor
72266-234-25 | 15 mg/mL, 1 mL single-dose vial | 25 vials per carton
72266-118-25 | 30 mg/mL, 1 mL single-dose vial | 25 vials per carton
72266-119-25* | 60 mg/2 mL, 2 mL single-dose vial | 25 vials per carton

*FOR IM USE ONLY
Storage Conditions
Store at 20° to 25°C (68° to 77°F). [See USP Controlled Room Temperature.]

Protect from light. Retain in carton until time of use.

Distributed by:
Fosun Pharma USA Inc.
Princeton, NJ 08540
Made in India

Revised: 05/2023

Medication Guide for Non-Steroidal Anti-Inflammatory Drugs (NSAIDs)

What is the most important information I should know about medicines called Non-Steroidal Anti-Inflammatory Drugs (NSAIDs)?

NSAIDs can cause serious side effects, including:

• Increased risk of a heart attack or stroke that can lead to death.This risk may happen early in treatment and may increase:
o with increasing doses of NSAIDs
o with longer use of NSAIDs

Do not take NSAIDs right before or after a heart surgery called a"coronary artery bypass graft (CABG)."
Avoid taking NSAIDs after a recent heart attack, unless your healthcare provider tells you to. You may have an increased risk of another heart attack if you take NSAIDs after a recent heart attack.

• Increased risk of bleeding, ulcers, and tears (perforation) of the esophagus (tube leading from the mouth to the stomach), stomach and intestines:
•anytime during use
•without warning symptoms
•that may cause death

The risk of getting an ulcer or bleeding increases with:
•past history of stomach ulcers, or stomach or intestinal bleeding with the use of NSAIDs
•taking medicines called "corticosteroids","anticoagulants", "SSRIs", or "SNRIs"
•increasing doses of NSAIDs
•longer use of NSAIDs
•smoking
•drinking alcohol
•older age
•poor health
•advanced liver disease
•bleeding problems

NSAIDs should only be used:
•exactly as prescribed
•at the lowest dose possible for your treatment
•for the shortest time needed

What are NSAIDs?
NSAIDs are used to treat pain and redness, swelling, and heat (inflammation) from medical conditions such as different types of arthritis, menstrual cramps, and other types of short-term pain.

Who should not take NSAIDs?
Do not take NSAIDs:
• if you had an asthma attack, hives, or other allergic reaction with aspirin or any other NSAIDs.
• right before or after heart bypass surgery.
Before taking NSAIDs, tell your healthcare provider about all of your medical conditions, including if you:
• have liver or kidney problems
• have high blood pressure
• have asthma
• are pregnant or plan to become pregnant. Taking NSAIDs at about 20 weeks of pregnancy or later may harm your unborn baby. If you need to take NSAIDs for more than 2 days when you are between 20 and 30 weeks of pregnancy, your healthcare provider may need to monitor the amount of fluid in your womb around your baby. You should not take NSAIDs after about 30 weeks of pregnancy.

• are breastfeeding or plan to breast feed.

Tell your healthcare provider about all of the medicines you take, including prescription or over-the-counter medicines, vitamins or herbalsupplements.NSAIDs and some other medicines can interact with each other and cause serious side effects. Do not start taking any new medicine without talking to your healthcare provider first.

What are the possible side effects of NSAIDs?
NSAIDs can cause serious side effects, including:
See "What is the most important information I should know about medicines called Non-Steroidal Anti-Inflammatory Drugs (NSAIDs) ?"
• new or worse high blood pressure
• heart failure
• liver problems including liver failure
• kidney problems including kidney failure
• low red blood cells (anemia)
• life-threatening skin reactions
• life-threatening allergic reactions
• Other side effects of NSAIDs include:stomach pain, constipation, diarrhea, gas, heartburn, nausea, vomiting, and dizziness.

Get emergency help right away if you get any of the following symptoms:
• shortness of breath or trouble breathing
• chest pain
• weakness in one part or side of your body
• slurred speech
• swelling of the face or throat

Stop taking your NSAID and call your healthcare provider right away if you get any of the following symptoms:
• nausea
• more tired or weaker than usual
• diarrhea
• itching
• your skin or eyes look yellow
• indigestion or stomach pain
• flu-like symptoms
• vomit blood
• there is blood in your bowel movement or it is black and sticky like tar
• unusual weight gain
• skin rash or blisters with fever
• swelling of the arms and legs, hands and feet

If you take too much of your NSAID, call your healthcare provider or get medical help right away.
These are not all the possible side effects of NSAIDs. For more information, ask your healthcare provider or pharmacist about NSAIDs.

Call your doctor for medical advice about side effects. You may report side effects to FDA at 1-800-FDA-1088.

Other information about NSAIDs
• Aspirin is an NSAID medicine but it does not increase the chance of a heart attack. Aspirin can cause bleeding in the brain, stomach, and intestines. Aspirin can also cause ulcers in the stomach and intestines.
• Some NSAIDs are sold in lower doses without a prescription (over-the-counter). Talk to your healthcare provider before using over-the-counter NSAIDs for more than 10 days.

General information about the safe and effective use of NSAIDs
Medicines are sometimes prescribed for purposes other than those listed in a Medication Guide. Do not use NSAIDs for a condition for which it was not prescribed. Do not give NSAIDs to other people, even if they have the same symptoms that you have. It may harm them.
If you would like more information about NSAIDs, talk with your healthcare provider. You can ask your pharmacist or healthcare provider for information about NSAIDs that is written for health professionals.
This Medication Guide has been approved by the U.S. Food and Drug Administration.

Distributed by:
Fosun Pharma USA Inc.
Princeton, NJ 08540
Made in India
Revised: 05/2023

Lidocaine Hydrochloride Injection, USP

For Infiltration and Nerve Block

Rx only

DESCRIPTION

Lidocaine hydrochloride injection, USP is sterile, nonpyrogenic, aqueous solution that contains a local anesthetic agent and is administered parenterally by injection. See INDICATIONS AND USAGEsection for specific uses.
Lidocaine hydrochloride injection, USP contains lidocaine hydrochloride, which is chemically designated as acetamide, 2-(diethylamino)-N-(2,6-dimethylphenyl)-, monohydrochloride and has the molecular weight 270.8. Lidocaine hydrochloride (C14H22N2O • HCl) has the following structural formula:

Lidocaine hydrochloride injection, USP is a sterile, nonpyrogenic, isotonic solution containing sodium chloride. The pH of the solution is adjusted to approximately 6.5 (5.0 to 7.0) with sodium hydroxide and/or hydrochloric acid.

CLINICAL PHARMACOLOGY

Mechanism of Action

Lidocaine stabilizes the neuronal membrane by inhibiting the ionic fluxes required for the initiation and conduction of impulses thereby effecting local anesthetic action.

Hemodynamics

Excessive blood levels may cause changes in cardiac output, total peripheral resistance, and mean arterial pressure. With central neural blockade these changes may be attributable to block of autonomic fibers, a direct depressant effect of the local anesthetic agent on various components of the cardiovascular system, and/or the beta-adrenergic receptor stimulating action of epinephrine when present. The net effect is normally a modest hypotension when the recommended dosages are not exceeded.

Pharmacokinetics and Metabolism

Information derived from diverse formulations, concentrations and usages reveals that lidocaine is completely absorbed following parenteral administration, its rate of absorption depending, for example, upon various factors such as the site of administration and the presence or absence of a vasoconstrictor agent. Except for intravascular administration, the highest blood levels are obtained following intercostal nerve block and the lowest after subcutaneous administration.
The plasma binding of lidocaine is dependent on drug concentration, and the fraction bound decreases with increasing concentration. At concentrations of 1 to 4 mcg of free base per mL 60 to 80 percent of lidocaine is protein bound. Binding is also dependent on the plasma concentration of the alpha-1-acid glycoprotein.
Lidocaine crosses the blood-brain and placental barriers, presumably by passive diffusion.
Lidocaine is metabolized rapidly by the liver, and metabolites and unchanged drug are excreted by the kidneys. Biotransformation includes oxidative N-dealkylation, ring hydroxylation, cleavage of the amide linkage, and conjugation. N-dealkylation, a major pathway of biotransformation, yields the metabolites monoethylglycinexylidide and glycinexylidide. The pharmacological/toxicological actions of these metabolites are similar to, but less potent than, those of lidocaine. Approximately 90% of lidocaine administered is excreted in the form of various metabolites, and less than 10% is excreted unchanged. The primary metabolite in urine is a conjugate of 4-hydroxy-2,6-dimethylaniline.
The elimination half-life of lidocaine following an intravenous bolus injection is typically 1.5 to 2 hours. Because of the rapid rate at which lidocaine is metabolized, any condition that affects liver function may alter lidocaine kinetics. The half-life may be prolonged two-fold or more in patients with liver dysfunction. Renal dysfunction does not affect lidocaine kinetics but may increase the accumulation of metabolites.
Factors such as acidosis and the use of CNS stimulants and depressants affect the CNS levels of lidocaine required to produce overt systemic effects. Objective adverse manifestations become increasingly apparent with increasing venous plasma levels above 6 mcg free base per mL. In the rhesus monkey arterial blood levels of 18 to 21 mcg/mL have been shown to be threshold for convulsive activity.

INDICATIONS AND USAGE

Lidocaine hydrochloride injection is indicated for production of local or regional anesthesia by infiltration techniques such as percutaneous injection and intravenous regional anesthesia by peripheral nerve block techniques such as brachial plexus and intercostal and by central neural techniques such as lumbar and caudal epidural blocks, when the accepted procedures for these techniques as described in standard textbooks are observed.

CONTRAINDICATIONS

Lidocaine hydrochloride is contraindicated in patients with a known history of hypersensitivity to local anesthetics of the amide type.

WARNINGS

LIDOCAINE HYDROCHLORIDE INJECTION FOR INFILTRATION AND NERVE BLOCK SHOULD BE EMPLOYED ONLY BY CLINICIANS WHO ARE WELL VERSED IN DIAGNOSIS AND MANAGEMENT OF DOSE-RELATED TOXICITY AND OTHER ACUTE EMERGENCIES THAT MIGHT ARISE FROM THE BLOCK TO BE EMPLOYED AND THEN ONLY AFTER ENSURING THE IMMEDIATEAVAILABILITY OF OXYGEN, OTHER RESUSCITATIVE DRUGS, CARDIOPULMONARY EQUIPMENT AND THE PERSONNEL NEEDED FOR PROPER MANAGEMENT OF TOXIC REACTIONS AND RELATED EMERGENCIES (see also ADVERSE REACTIONSand PRECAUTIONS). DELAY IN PROPER MANAGEMENT OF DOSE-RELATED TOXICITY, UNDERVENTILATION FROM ANY CAUSE AND/OR ALTERED SENSITIVITY MAY LEAD TO THE DEVELOPMENT OF ACIDOSIS, CARDIAC ARREST AND, POSSIBLY, DEATH.
Methemoglobinemia
Cases of methemoglobinemia have been reported in association with local anesthetic use. Although all patients are at risk for methemoglobinemia, patients with glucose-6-phosphate dehydrogenase deficiency, congenital or idiopathic methemoglobinemia, cardiac or pulmonary compromise, infants under 6 months of age, and concurrent exposure to oxidizing agents or their metabolites are more susceptible to developing clinical manifestations of the condition. If local anesthetics must be used in these patients, close monitoring for symptoms and signs of methemoglobinemia is recommended.
Signs of methemoglobinemia may occur immediately or may be delayed some hours after exposure, and are characterized by a cyanotic skin discoloration and/or abnormal coloration of the blood. Methemoglobin levels may continue to rise; therefore, immediate treatment is required to avert more serious central nervous system and cardiovascular adverse effects, including seizures, coma, arrhythmias, and death. Discontinue lidocaine hydrochloride and any other oxidizing agents. Depending on the severity of the signs and symptoms, patients may respond to supportive care, i.e., oxygen therapy, hydration. A more severe clinical presentation may require treatment with methylene blue, exchange transfusion, or hyperbaric oxygen.
Intra-articular infusions of local anesthetics following arthroscopic and other surgical procedures is an unapproved use, and there have been postmarketing reports of chondrolysis in patients receiving such infusions. The majority of reported cases of chondrolysis have involved the shoulder joint; cases of gleno-humeral chondrolysis have been described in pediatric and adult patients following intra-articular infusions of local anesthetics with and without epinephrine for periods of 48 to 72 hours. There is insufficient information to determine whether shorter infusion periods are not associated with these findings. The time of onset of symptoms, such as joint pain, stiffness and loss of motion can be variable, but may begin as early as the 2ndmonth after surgery. Currently, there is no effective treatment for chondrolysis; patients who experienced chondrolysis have required additional diagnostic and therapeutic procedures and some required arthroplasty or shoulder replacement.
To avoid intravascular injection, aspiration should be performed before the local anesthetic solution is injected. The needle must be repositioned until no return of blood can be elicited by aspiration. Note, however, that the absence of blood in the syringe does not guarantee that intravascular injection has been avoided.
Anaphylactic reactions may occur following administration of lidocaine hydrochloride (see ADVERSE REACTIONS).
In the case of severe reaction, discontinue the use of the drug.

PRECAUTIONS

General

The safety and effectiveness of lidocaine hydrochloride depend on proper dosage, correct technique, adequate precautions, and readiness for emergencies. Standard textbooks should be consulted for specific techniques and precautions for various regional anesthetic procedures.
Resuscitative equipment, oxygen, and other resuscitative drugs should be available for immediate use (see WARNINGSand ADVERSE REACTIONS). The lowest dosage that results in effective anesthesia should be used to avoid high plasma levels and serious adverse effects. Syringe aspirations should also be performed before and during each supplemental injection when using indwelling catheter techniques. During the administration of epidural anesthesia, it is recommended that a test dose be administered initially and that the patient be monitored for central nervous system toxicity and cardiovascular toxicity, as well as for signs of unintended intrathecal administration, before proceeding. When clinical conditions permit, consideration should be given to employing local anesthetic solutions that contain epinephrine for the test dose because circulatory changes compatible with epinephrine may also serve as a warning sign of unintended intravascular injection. An intravascular injection is still possible even if aspirations for blood are negative. Repeated doses of lidocaine hydrochloride may cause significant increases in blood levels with each repeated dose because of slow accumulation of the drug or its metabolites. Tolerance to elevated blood levels varies with the status of the patient. Debilitated, elderly patients, acutely ill patients, and children should be given reduced doses commensurate with their age and physical condition. Lidocaine hydrochloride should also be used with caution in patients with severe shock or heart block.
Lumbar and caudal epidural anesthesia should be used with extreme caution in persons with the following conditions: existing neurological disease, spinal deformities, septicemia, and severe hypertension.
Local anesthetic solutions containing a vasoconstrictor should be used cautiously and in carefully circumscribed quantities in areas of the body supplied by end arteries or having otherwise compromised blood supply. Patients with peripheral vascular disease and those with hypertensive vascular disease may exhibit exaggerated vasoconstrictor response. Ischemic injury or necrosis may result. Preparations containing a vasoconstrictor should be used with caution in patients during or following the administration of potent general anesthetic agents, since cardiac arrhythmias may occur under such conditions.
Careful and constant monitoring of cardiovascular and respiratory (adequacy of ventilation) vital signs and the patient’s state of consciousness should be accomplished after each local anesthetic injection. It should be kept in mind at such times that restlessness, anxiety, tinnitus, dizziness, blurred vision, tremors, depression or drowsiness may be early warning signs of central nervous system toxicity.
Since amide-type local anesthetics are metabolized by the liver, lidocaine hydrochloride injection should be used with caution in patients with hepatic disease. Patients with severe hepatic disease, because of their inability to metabolize local anesthetics normally, are at greater risk of developing toxic plasma concentrations. Lidocaine hydrochloride injection should also be used with caution in patients with impaired cardiovascular function since they may be less able to compensate for functional changes associated with the prolongation of A-V conduction produced by these drugs.
Many drugs used during the conduct of anesthesia are considered potential triggering agents for familial malignant hyperthermia. Since it is not known whether amide-type local anesthetics may trigger this reaction and since the need for supplemental general anesthesia cannot be predicted in advance, it is suggested that a standard protocol for the management of malignant hyperthermia should be available. Early unexplained signs of tachycardia, tachypnea, labile blood pressure and metabolic acidosis may precede temperature elevation. Successful outcome is dependent on early diagnosis, prompt discontinuance of the suspect triggering agent(s) and institution of treatment, including oxygen therapy, indicated supportive measures and dantrolene (consult dantrolene sodium intravenous package insert before using).
Proper tourniquet technique, as described in publications and standard textbooks, is essential in the performance of intravenous regional anesthesia. Solutions containing epinephrine or other vasoconstrictors should not be used for this technique.
Lidocaine hydrochloride should be used with caution in persons with known drug sensitivities. Patients allergic to para-aminobenzoic acid derivatives (procaine, tetracaine, benzocaine, etc.) have not shown cross sensitivity to lidocaine hydrochloride.

Use in the Head and Neck Area

Small doses of local anesthetics injected into the head and neck area, including retrobulbar, dental and stellate ganglion blocks, may produce adverse reactions similar to systemic toxicity seen with unintentional intravascular injections of larger doses. Confusion, convulsions, respiratory depression and/or respiratory arrest, and cardiovascular stimulation or depression have been reported. These reactions may be due to intra-arterial injection of the local anesthetic with retrograde flow to the cerebral circulation. Patients receiving these blocks should have their circulation and respiration monitored and be constantly observed. Resuscitative equipment and personnel for treating adverse reactions should be immediately available. Dosage recommendations should not be exceeded (see DOSAGE AND ADMINISTRATION).

Information for Patients

When appropriate, patients should be informed in advance that they may experience temporary loss of sensation and motor activity, usually in the lower half of the body, following proper administration of epidural anesthesia.
Inform patients that use of local anesthetics may cause methemoglobinemia, a serious condition that must be treated promptly. Advise patients or caregivers to seek immediate medical attention if they or someone in their care experience the following signs or symptoms: pale, gray, or blue colored skin (cyanosis); headache; rapid heart rate; shortness of breath; lightheadedness; or fatigue.

Clinically Significant Drug Interactions

The administration of local anesthetic solutions containing epinephrine or norepinephrine to patients receiving monoamine oxidase inhibitors or tricyclic antidepressants may produce severe, prolonged hypertension.
Phenothiazines and butyrophenones may reduce or reverse the pressor effect of epinephrine.
Concurrent use of these agents should generally be avoided. In situations when concurrent therapy is necessary, careful patient monitoring is essential.
Concurrent administration of vasopressor drugs (for the treatment of hypotension related to obstetric blocks) and ergot-type oxytocic drugs may cause severe, persistent hypertension or cerebrovascular accidents.

Drug/Laboratory Test Interactions

The intramuscular injection of lidocaine hydrochloride may result in an increase in creatine phosphokinase levels. Thus, the use of this enzyme determination, without isoenzyme separation, as a diagnostic test for the presence of acute myocardial infarction may be compromised by the intramuscular injection of lidocaine hydrochloride.
Patients who are administered local anesthetics are at increased risk of developing methemoglobinemia when concurrently exposed to the following drugs, which could include other local anesthetics:
Examples of Drugs Associated with Methemoglobinemia:

Class | Examples
Nitrates/Nitrites | nitric oxide, nitroglycerin, nitroprusside, nitrous oxide
Local anesthetics | articaine, benzocaine, bupivacaine, lidocaine, mepivacaine, prilocaine, procaine, ropivacaine, tetracaine
Antineoplastic agents | cyclophosphamide, flutamide, hydroxyurea, ifosfamide, rasburicase
Antibiotics | dapsone, nitrofurantoin, para-aminosalicylic acid, sulfonamides
Antimalarials | chloroquine, primaquine
Anticonvulsants | Phenobarbital, phenytoin, sodium valproate
Other drugs | acetaminophen, metoclopramide, quinine, sulfasalazine

Carcinogenesis, Mutagenesis, Impairment of Fertility

Studies of lidocaine hydrochloride in animals to evaluate the carcinogenic and mutagenic potential or the effect on fertility have not been conducted.

Pregnancy

Teratogenic Effects

Reproduction studies have been performed in rats at doses up to 6.6 times the human dose and have revealed no evidence of harm to the fetus caused by lidocaine hydrochloride. There are, however, no adequate and well-controlled studies in pregnant women. Animal reproduction studies are not always predictive of human response. General consideration should be given to this fact before administering lidocaine hydrochloride to women of childbearing potential, especially during early pregnancy when maximum organogenesis takes place.

Labor and Delivery

Local anesthetics rapidly cross the placenta and when used for epidural, paracervical, pudendal or caudal block anesthesia, can cause varying degrees of maternal, fetal and neonatal toxicity see CLINICAL PHARMACOLOGY, Pharmacokinetics and Metabolism). The potential for toxicity depends upon the procedure performed, the type and amount of drug used, and the technique of drug administration. Adverse reactions in the parturient, fetus and neonate involve alterations of the central nervous system, peripheral vascular tone and cardiac function.
Maternal hypotension has resulted from regional anesthesia. Local anesthetics produce vasodilation by blocking sympathetic nerves. Elevating the patient’s legs and positioning her on her left side will help prevent decreases in blood pressure.
The fetal heart rate also should be monitored continuously, and electronic fetal monitoring is highly advisable.
Epidural, spinal, paracervical, or pudendal anesthesia may alter the forces of parturition through changes in uterine contractility or maternal expulsive efforts. In one study, paracervical block anesthesia was associated with a decrease in the mean duration of first stage labor and facilitation of cervical dilation. However, spinal and epidural anesthesia have also been reported to prolong the second stage of labor by removing the parturient’s reflex urge to bear down or by interfering with motor function. The use of obstetrical anesthesia may increase the need for forceps assistance.
The use of some local anesthetic drug products during labor and delivery may be followed by diminished muscle strength and tone for the first day or two of life. The long-term significance of these observations is unknown. Fetal bradycardia may occur in 20 to 30 percent of patients receiving paracervical nerve block anesthesia with the amide-type local anesthetics and may be associated with fetal acidosis. Fetal heart rate should always be monitored during paracervical anesthesia. The physician should weigh the possible advantages against risks when considering a paracervical block in prematurity, toxemia of pregnancy, and fetal distress. Careful adherence to recommended dosage is of the utmost importance in obstetrical paracervical block. Failure to achieve adequate analgesia with recommended doses should arouse suspicion of intravascular or fetal intracranial injection. Cases compatible with unintended fetal intracranial injection of local anesthetic solution have been reported following intended paracervical or pudendal block or both. Babies so affected present with unexplained neonatal depression at birth, which correlates with high local anesthetic serum levels, and often manifest seizures within six hours. Prompt use of supportive measures combined with forced urinary excretion of the local anesthetic has been used successfully to manage this complication.
Case reports of maternal convulsions and cardiovascular collapse following use of some local anesthetics for paracervical block in early pregnancy (as anesthesia for elective abortion) suggest that systemic absorption under these circumstances may be rapid. The recommended maximum dose of each drug should not be exceeded. Injection should be made slowly and with frequent aspiration. Allow a 5-minute interval between sides.

Nursing Mothers

It is not known whether this drug is excreted in human milk. Because many drugs are excreted in human milk, caution should be exercised when lidocaine hydrochloride is administered to a nursing woman.

Pediatric Use

Dosages in children should be reduced, commensurate with age, body weight and physical condition, see DOSAGE AND ADMINISTRATION.

ADVERSE REACTIONS

Systemic

Adverse experiences following the administration of lidocaine hydrochloride are similar in nature to those observed with other amide local anesthetic agents. These adverse experiences are, in general, dose-related and may result from high plasma levels caused by excessive dosage, rapid absorption or inadvertent intravascular injection, or may result from a hypersensitivity, idiosyncrasy or diminished tolerance on the part of the patient. Serious adverse experiences are generally systemic in nature. The following types are those most commonly reported:

Central Nervous System

CNS manifestations are excitatory and/or depressant and may be characterized by lightheadedness, nervousness, apprehension, euphoria, confusion, dizziness, drowsiness, tinnitus, blurred or double vision, vomiting, sensations of heat, cold or numbness, twitching, tremors, convulsions, unconsciousness, respiratory depression and arrest. The excitatory manifestations may be very brief or may not occur at all, in which case the first manifestation of toxicity may be drowsiness merging into unconsciousness and respiratory arrest.

Drowsiness following the administration of lidocaine hydrochloride is usually an early sign of a high blood level of the drug and may occur as a consequence of rapid absorption.

Cardiovascular System

Cardiovascular manifestations are usually depressant and are characterized by bradycardia, hypotension, and cardiovascular collapse, which may lead to cardiac arrest.

Allergic

Allergic reactions are characterized by cutaneous lesions, urticaria, edema or anaphylactoid reactions. Allergic reactions may occur as a result of sensitivity to local anesthetic agents. Allergic reactions, including anaphylactic reactions, may occur as a result of sensitivity to lidocaine, but are infrequent. If allergic reactions do occur, they should be managed by conventional means. The detection of sensitivity by skin testing is of doubtful value.
There have been no reports of cross sensitivity between lidocaine hydrochloride and procainamide or between lidocaine hydrochloride and quinidine.

Neurologic

The incidences of adverse reactions associated with the use of local anesthetics may be related to the total dose of local anesthetic administered and are also dependent upon the particular drug used, the route of administration and the physical status of the patient. In a prospective review of 10,440 patients who received lidocaine hydrochloride for spinal anesthesia, the incidences of adverse reactions were reported to be about 3 percent each for positional headaches, hypotension and backache; 2 percent for shivering; and less than 1 percent each for peripheral nerve symptoms, nausea, respiratory inadequacy and double vision. Many of these observations may be related to local anesthetic techniques, with or without a contribution from the local anesthetic.
In the practice of caudal or lumbar epidural block, occasional unintentional penetration of the subarachnoid space by the catheter may occur. Subsequent adverse effects may depend partially on the amount of drug administered subdurally. These may include spinal block of varying magnitude (including total spinal block), hypotension secondary to spinal block, loss of bladder and bowel control, and loss of perineal sensation and sexual function. Persistent motor, sensory and/or autonomic (sphincter control) deficit of some lower spinal segments with slow recovery (several months) or incomplete recovery have been reported in rare instances when caudal or lumbar epidural block has been attempted. Backache and headache have also been noted following use of these anesthetic procedures.
There have been reported cases of permanent injury to extraocular muscles requiring surgical repair following retrobulbar administration.

Hematologic

Methemoglobinemia.

OVERDOSAGE

Acute emergencies from local anesthetics are generally related to high plasma levels encountered during therapeutic use of local anesthetics or to unintended subarachnoid injection of local anesthetic solution (see ADVERSE REACTIONS, WARNINGS, and PRECAUTIONS).

Management of Local Anesthetic Emergencies

The first consideration is prevention, best accomplished by careful and constant monitoring of cardiovascular and respiratory vital signs and the patient’s state of consciousness after each local anesthetic injection. At the first sign of change, oxygen should be administered.
The first step in the management of convulsions, as well as underventilation or apnea due to unintended subarachnoid injection of drug solution, consists of immediate attention to the maintenance of a patent airway and assisted or controlled ventilation with oxygen and a delivery system capable of permitting immediate positive airway pressure by mask. Immediately after the institution of these ventilatory measures, the adequacy of the circulation should be evaluated, keeping in mind that drugs used to treat convulsions sometimes depress the circulation when administered intravenously. Should convulsions persist despite adequate respiratory support, and if the status of the circulation permits, small increments of an ultra-short acting barbiturate (such as thiopental or thiamylal) or a benzodiazepine (such as diazepam) may be administered intravenously. The clinician should be familiar, prior to the use of local anesthetics, with these anticonvulsant drugs. Supportive treatment of circulatory depression may require administration of intravenous fluids and, when appropriate, a vasopressor as directed by the clinical situation (e.g., ephedrine).
If not treated immediately, both convulsions and cardiovascular depression can result in hypoxia, acidosis, bradycardia, arrhythmias and cardiac arrest. Underventilation or apnea due to unintentional subarachnoid injection of local anesthetic solution may produce these same signs and also lead to cardiac arrest if ventilatory support is not instituted. If cardiac arrest should occur, standard cardiopulmonary resuscitative measures should be instituted.
Endotracheal intubation, employing drugs and techniques familiar to the clinician, may be indicated, after initial administration of oxygen by mask, if difficulty is encountered in the maintenance of a patent airway or if prolonged ventilatory support (assisted or controlled) is indicated.
Dialysis is of negligible value in the treatment of acute overdosage with lidocaine hydrochloride.
The oral LD50of lidocaine hydrochloride in non-fasted female rats is 459 (346 to 773) mg/kg (as the salt) and 214 (159 to 324) mg/kg (as the salt) in fasted female rats.

DOSAGE AND ADMINISTRATION

Table 1 (Recommended Dosages) summarizes the recommended volumes and concentrations of lidocaine hydrochloride injection for various types of anesthetic procedures. The dosages suggested in this table are for normal healthy adults and refer to the use of epinephrine-free solutions. When larger volumes are required, only solutions containing epinephrine should be used except in those cases where vasopressor drugs may be contraindicated.

There have been adverse event reports of chondrolysis in patients receiving intra-articular infusions of local anesthetics following arthroscopic and other surgical procedures. Lidocaine hydrochloride injection is not approved for this use (see WARNINGSand DOSAGE AND ADMINISTRATION).
These recommended doses serve only as a guide to the amount of anesthetic required for most routine procedures. The actual volumes and concentrations to be used depend on a number of factors such as type and extent of surgical procedure, depth of anesthesia and degree of muscular relaxation required, duration of anesthesia required, and the physical condition of the patient. In all cases the lowest concentration and smallest dose that will produce the desired result should be given. Dosages should be reduced for children and for the elderly and debilitated patients and patients with cardiac and/or liver disease.
The onset of anesthesia, the duration of anesthesia and the degree of muscular relaxation are proportional to the volume and concentration (i.e., total dose) of local anesthetic used. Thus, an increase in volume and concentration of lidocaine hydrochloride injection will decrease the onset of anesthesia, prolong the duration of anesthesia, provide a greater degree of muscular relaxation and increase the segmental spread of anesthesia. However, increasing the volume and concentration of lidocaine hydrochloride injection may result in a more profound fall in blood pressure when used in epidural anesthesia. Although the incidence of side effects with lidocaine hydrochloride is quite low, caution should be exercised when employing large volumes and concentrations, since the incidence of side effects is directly proportional to the total dose of local anesthetic agent injected.

Epidural Anesthesia

For epidural anesthesia, only the following dosage forms of lidocaine hydrochloride injection are recommended:
1% without epinephrine 5 mL ampules
2% without epinephrine 2 mL ampules
Although these solutions are intended specifically for epidural anesthesia, they may also be used for infiltration and peripheral nerve block, provided they are employed as single dose units. These solutions contain no bacteriostatic agent.
In epidural anesthesia, the dosage varies with the number of dermatomes to be anesthetized (generally 2 to 3 mL of the indicated concentration per dermatome).

Caudal and Lumbar Epidural Block

As a precaution against the adverse experience sometimes observed following unintentional penetration of the subarachnoid space, a test dose such as 2 to 3 mL of 1.5% lidocaine hydrochloride should be administered at least 5 minutes prior to injecting the total volume required for a lumbar or caudal epidural block. The test dose should be repeated if the patient is moved in a manner that may have displaced the catheter. Epinephrine, if contained in the test dose (10 to 15 mcg have been suggested), may serve as a warning of unintentional intravascular injection. If injected into a blood vessel, this amount of epinephrine is likely to produce a transient “epinephrine response” within 45 seconds, consisting of an increase in heart rate and systolic blood pressure, circumoral pallor, palpitations and nervousness in the unsedated patient. The sedated patient may exhibit only a pulse rate increase of 20 or more beats per minute for 15 or more seconds. Patients on beta blockers may not manifest changes in heart rate, but blood pressure monitoring can detect an evanescent rise in systolic blood pressure. Adequate time should be allowed for onset of anesthesia after administration of each test dose. The rapid injection of a large volume of lidocaine hydrochloride injection through the catheter should be avoided, and, when feasible, fractional doses should be administered.
In the event of the known injection of a large volume of local anesthetic solution into the subarachnoid space, after suitable resuscitation and if the catheter is in place, consider attempting the recovery of drug by draining a moderate amount of cerebrospinal fluid (such as 10 mL) through the epidural catheter.

MAXIMUM RECOMMENDED DOSAGES

Adults

For normal healthy adults, the maximum individual dose should not exceed 4.5 mg/kg (2 mg/lb) of body weight, and in general it is recom mended that the max i m um t otal dose does not exceed 300 mg. For continuous epidural or caudal anesthesia, the maximum recommended dosage should not be administered at intervals of less than 90 minutes. When continuous lumbar or caudal epidural anesthesia is used for non-obstetrical procedures, more drug may be administered if required to produce adequate anesthesia.
The maximum recommended dose per 90 minute period of lidocaine hydrochloride for paracervical block in obstetrical patients and non-obstetrical patients is 200 mg total. One half of the total dose is usually administered to each side. Inject slowly, five minutes between sides (see also discussion of paracervical block in PRECAUTIONS).
For intravenous regional anesthesia, the dose administered should not exceed 4 mg/kg in adults.

Children

It is difficult to recommend a maximum dose of any drug for children, since this varies as a function of age and weight. For children over 3 years of age who have a normal lean body mass and normal body development, the maximum dose is determined by the child’s age and weight. For example, in a child of 5 years weighing 50 lbs the dose of lidocaine hydrochloride should not exceed 75 to 100 mg (1.5 to 2 mg/lb). The use of even more dilute solutions (i.e., 0.25 to 0.5%) and total dosages not to exceed 3 mg/kg (1.4 mg/lb) are recommended for induction of intravenous regional anesthesia in children.
In order to guard against systemic toxicity, the lowest effective concentration and lowest effective dose should be used at all times. In some cases it will be necessary to dilute available concentrations with 0.9% sodium chloride injection in order to obtain the required final concentration.
NOTE: Parenteral drug products should be inspected visually for particulate matter and discoloration prior to administration whenever the solution and container permit. Do not use if solution is discolored or contains a precipitate.

Table 1: Recommended Dosages
Procedure | Lidocaine Hydrochloride Injection (without epinephrine)
Procedure | Conc (%) | Vol (mL) | Total Dose (mg)
Infiltration
Percutaneous | 0.5 or 1 | 1 to 60 | 5 to 300
Intravenous regional | 0.5 | 10 to 60 | 50 to 300
Peripheral Nerve Blocks, e.g.,
Brachial | 1.5 | 15 to 20 | 225 to 300
Dental | 2 | 1 to 5 | 20 to 100
Intercostal | 1 | 3 | 30
Paravertebral | 1 | 3 to 5 | 30 to 50
Pudendal (each side) | 1 | 10 | 100
Paracervical
Obstetrical analgesia (each side) | 1 | 10 | 100
Sympathetic Nerve Blocks, e.g.,
Cervical (stellate ganglion) | 1 | 5 | 50
Lumbar | 1 | 5 to 10 | 50 to 100
Central Neural Blocks
Epidural*
Thoracic | 1 | 20 to 30 | 200 to 300
Lumbar
Analgesia | 1 | 25 to 30 | 250 to 300
Anesthesia | 1.5 | 15 to 20 | 225 to 300
 | 2 | 10 to 15 | 200 to 300
Caudal
Obstetrical analgesia | 1 | 20 to 30 | 200 to 300
Surgical anesthesia | 1.5 | 15 to 20 | 225 to 300
*Dose determined by number of dermatomes to be anesthetized (2 to 3 mL/dermatome).

THE ABOVE SUGGESTED CONCENTRATIONS AND VOLUMES SERVE ONLY AS A GUIDE. OTHER VOLUMES AND CONCENTRATIONS MAY BE USED PROVIDED THE TOTAL MAXIMUM RECOMMENDED DOSE IS NOT EXCEEDED.

STERILIZATION, STORAGE AND TECHNICAL PROCEDURES

Disinfecting agents containing heavy metals, which cause release of respective ions (mercury, zinc, copper, etc.) should not be used for skin or mucous membrane disinfection as they have been related to incidents of swelling and edema.

HOW SUPPLIED

Lidocaine Hydrochloride Injection USP, is supplied as follows:
Lidocaine Hydrochloride Injection USP, 1% (10 mg/mL)
2 mL Ampules in a Carton of 10 NDC 55150-158-72
Sterile, Nonpyrogenic
Discard unused portion.
Store at 20° to 25°C (68° to 77°F) [see USP Controlled Room Temperature].
Distributed by:
AuroMedics Pharma LLC
279 Princeton-Hightstown Rd.
E. Windsor, NJ 08520
Manufactured by:
Eugia Pharma Specialities Limited
Hyderabad - 500032
India
Revised: October 2021

Active Ingredient Purpose

Povidone Iodine 10% w/v (9.85% w/w) Antiseptic

Purpose:

- First aid antiseptic to help prevent skin infection in minor cuts, scrapes and burns.
- For preparation of the skin prior to surgery.
- Helps reduce bacteria that can potentially cause skin infections.

Warnings:

- FOR EXTERNAL USE ONLY

Do not use:

- As a first aid antiseptic for more than 1 week.
- In the eyes.
- Over large areas of the body.

Ask a doctor before use if you have:

- Deep puncture wounds
- Animal bites
- Serious burns

Stop Use:

- If irritation and redness develop
- If condition persists for more than 72 hours, consult a physician.

Keep out of reach of children.If swallowed, get medical help or contact a Poison Control Center.

Directions Povidone iodine:

Tear at notch, remove applicator, use only once.

As a first aid antiseptic

- clean affected area
- apply 1 to 3 times daily
- may be covered with a sterile bandage, if bandaged let dry.

For preoperative patient skin preparation

- clean area
- apply to operative site prior to surgery using the applicator

Other information:

Store at room temperature.

Avoid excessive heat

INDICATIONS AND USAGE

For use as an

- first aid antiseptic
- pre-operative skin preperation

Inactive Ingredients

Inactive ingredients: Citric acid, glycerin, polysorbate 80, sodium citrate USP, sodium phosphate dibasic, water

Active ingredient

Isopropyl Alcohol 70% v/v

Purpose

Antiseptic

Uses

For first aid to decrease germs in

- minor cuts
- scrapes
- burns

For preparation of the skin prior to injection

Warnings

For external use only

Flammable - keep away from fire or flame

Do not use

with electrocautery procedures

When using this product do not

- get into eyes
- apply over large areas of the body
- in case of deep or puncture wounds, animal bites or serious burns consult a doctor

Stop use and ask a doctor if

- condition persists or gets worse or lasts for more than 72 hours
- do not use longer than 1 week unless directed by a doctor

Keep out of reach of children.

If swallowed, get medical help or contact a Poison Control Center right away.

Directions

- apply to skin as needed
- discard after single use

Other information

Protect from freezing and avoid excessive heat

Inactive ingredient

Water

PACKAGE LABEL

PRINCIPAL DISPLAY PANEL

NDC: 76420-771-01

RX Only

Ketorocaine-L™

Kit Contains

1 Ketorolac Tromethamine Inj., USP 30mg/mL (1mL)

1 Lidocaine HCl Injection, USP 1% Ampule (2mL)

1 Povidone-Iodine Swabsticks (3 Swabs)

2 Isopropyl Alcohol 70% Prep Pads

1 Pair Nitrile Powder Free Sterile Gloves (M)

1 Drape

1 Adhesive Bandage

5 Non Sterile 4x4 Gauze

Needles and Syringes Not Included

1 Dose

Single Use Only

Distributed by:

Enovachem™

PHARMACEUTICALS

Torrance, CA 90501